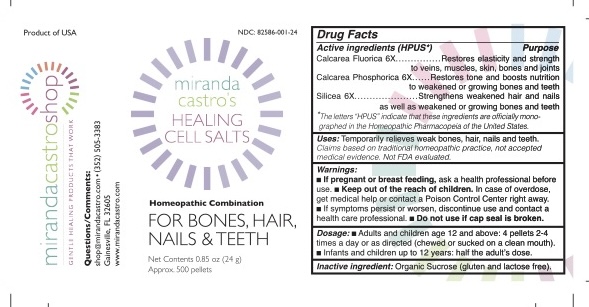 DRUG LABEL: Miranda Castros healing cell salts for bones, hair, nails and teeth
NDC: 82586-001 | Form: PELLET
Manufacturer: MIRANDA CASTRO'S SHOP, LLC
Category: homeopathic | Type: HUMAN OTC DRUG LABEL
Date: 20251023

ACTIVE INGREDIENTS: CALCIUM FLUORIDE 6 [hp_X]/1 1; TRIBASIC CALCIUM PHOSPHATE 6 [hp_X]/1 1; SILICON DIOXIDE 6 [hp_X]/1 1
INACTIVE INGREDIENTS: SUCROSE

MIRANDA CASTRO's healing cell salts Homeopathic Combination FOR BONES, HAIR, NAILS & TEETH

Active ingredients (HPUS*) | Purpose
Calcarea Fluorica 6X | Restores elasticity and strength to veins, muscles, skin, bones and joints
Calcarea Phosphorica 6X | Restores tone and boosts nutrition to weakened or growing bones and teeth
Silicea 6X | Strengthens weakened hair and nails as well as weakened or growing bones and teeth

*The letters "HPUS" indicate that these ingredients are officially monographed in the Homeopathic Pharmacopeia of the United States.

INDICATIONS AND USAGE

Uses:Temporarily relieves weak bones, hair, nails and teeth.

Claims based on traditional homeopathic practice, not accepted medical evidence. Not FDA evaluated.

Warnings:

- If pregnant or breast-feeding,ask a health care professional before use.
- Keep out of the reach of children.In case of overdose, get medical help or contact a Poison Control Center right away.
- If symptoms persist or worsen, discontinue use and contact a health care professional.
- Do not use if cap seal is broken.

Keep out of the reach of children.

Dosage:

- Adults and children age 12 and above: 4 pellets 2-4 times a day or as directed (chewed or sucked on a clean mouth).
- Infants and children up to 12 years: half the adult's dose.

Inactive ingredient: Organic Sucrose (gluten and lactose free).

Questions/Comments:shop@mirandacastro.com

(352) 505-3383

Gainesville, FL 32607

Product of USA

Manufactured for www.mirandacastroshop.com

PURPOSE

Homeopathic Combination FOR BONES, HAIR, NAILS and TEETH

PACKAGE LABEL

MIRANDA CASTRO's healing cell salts Homeopathic Combination FOR BONES, HAIR, NAILS and TEETH

Net Contents 0.85oz (24 g)

Approx. 500 pellets